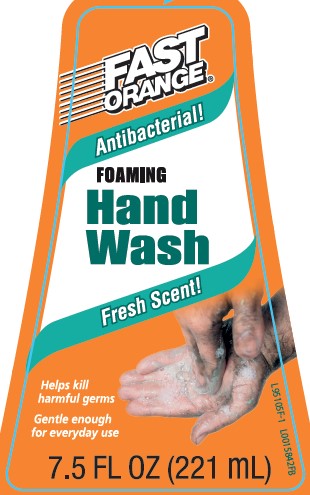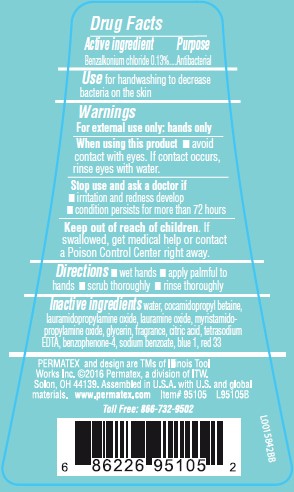 DRUG LABEL: Hand Wash
NDC: 70616-628 | Form: LIQUID
Manufacturer: Permatex
Category: otc | Type: HUMAN OTC DRUG LABEL
Date: 20260204

ACTIVE INGREDIENTS: BENZALKONIUM CHLORIDE 1.3 mg/1 mL
INACTIVE INGREDIENTS: WATER; COCAMIDOPROPYL BETAINE; LAURAMIDOPROPYLAMINE OXIDE; LAURAMINE OXIDE; MYRISTAMIDOPROPYLAMINE OXIDE; GLYCERIN; CITRIC ACID MONOHYDRATE; EDETATE SODIUM; SULISOBENZONE; SODIUM BENZOATE; FD&C BLUE NO. 1; D&C RED NO. 33

Fast Orange 628.002/628AD/AE
Antibacterial Hand Soap

Active ingredient

Benzalkonium chloride 0.13%

purpose

Antibacterial

Use

for handwashing to decrease bacteria on the skin

warnings

For external use only: hands only

When using this product

- avoid contact with eyes. If contact occurs, rinse eyes thoroughly with water.

Stop use and ask a doctor if

- irritation and redness develop
- condition persists for more than 72 hours

Keep out of reach of children

if swallowed, get medical help or contact a Poison Control Center right away.

Directions

- wet hands
- apply palmful to hands
- scrub thoroughly
- rinse thoroughly

Inactive ingredients

water, cocamidopropyl betaine, lauramidopropylamine oxide, lauramine oxide, myristamidopropylamine oxide, glycerin, fragrance, citric acid, tetrasodium EDTA, benzophenone-4, sodium benzoate, blue 1, red 33

ADVERSE REACTION

PERMATEX and design are TMs of Illinois Tool Works, Inc. ©2016 Permatex, a division of ITW.

Solon, OH 44139/ Assembled in U.S.A. with U.S. and global materials

www.permatex. com

Toll Free: 866-732-9502

Principal display panel

Fast Orange®

ANTIBACTERIAL!

FOAMING HAND SOAP

Fresh Scent!

Helps kill harmful germs

Gentle enough for everyday use

7.5 FL OZ (221 mL)